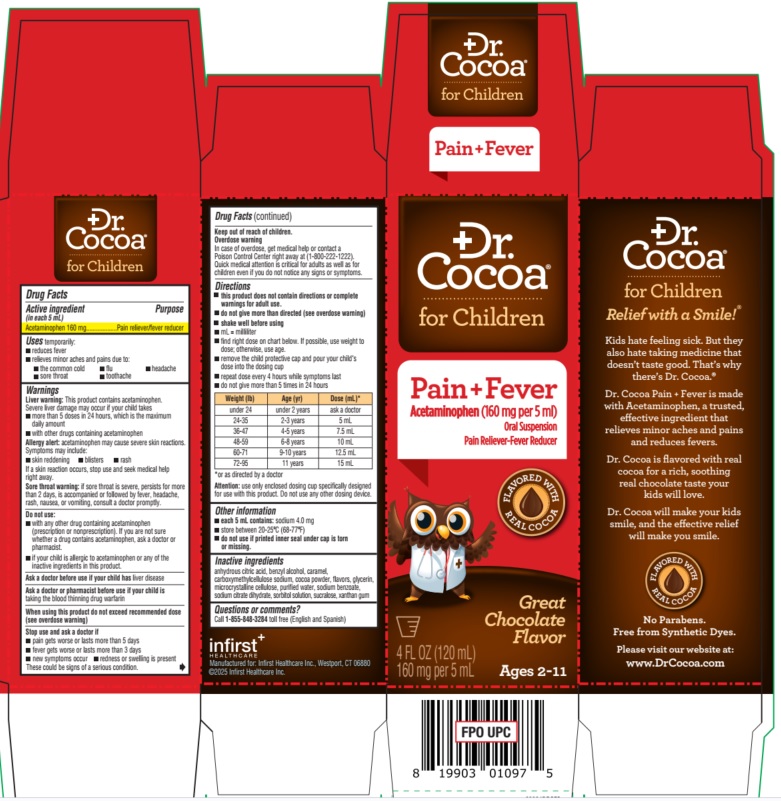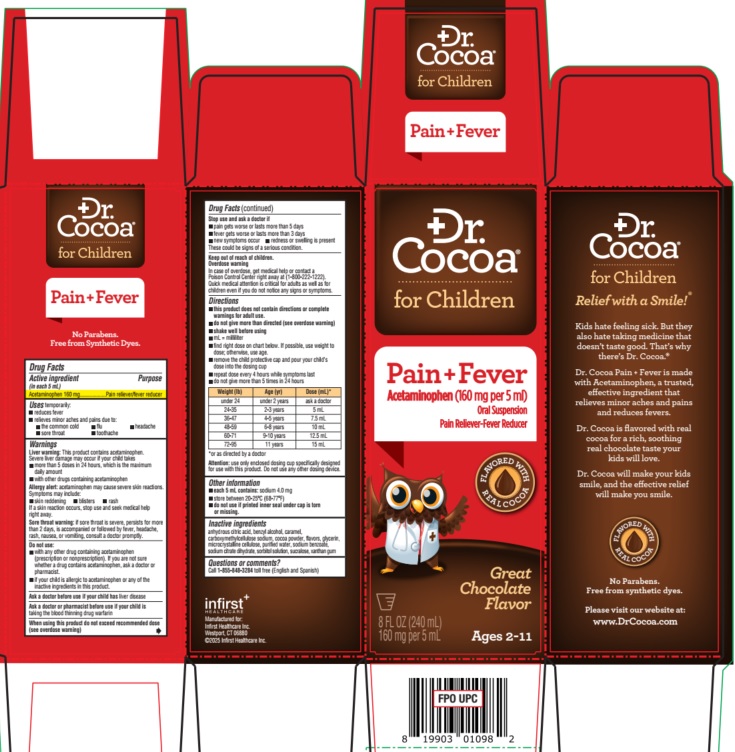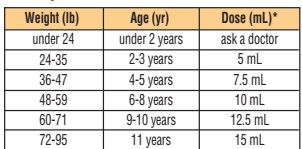 DRUG LABEL: Dr. Cocoa for Children
NDC: 62372-200 | Form: LIQUID
Manufacturer: Infirst Healthcare Inc.
Category: otc | Type: HUMAN OTC DRUG LABEL
Date: 20260101

ACTIVE INGREDIENTS: ACETAMINOPHEN 160 mg/5 mL
INACTIVE INGREDIENTS: MICROCRYSTALLINE CELLULOSE; CARBOXYMETHYLCELLULOSE SODIUM; THEOBROMA CACAO (COCOA) SEED POWDER; GLYCERIN; SODIUM BENZOATE; TRISODIUM CITRATE DIHYDRATE; WATER; SUCRALOSE; SORBITOL SOLUTION; XANTHAN GUM

Dr. Cocoa for Children, Pain & Fever

Active ingredient
(in each 5 mL)
Acetaminophen 160 mg

Purpose
Pain reliever/fever reducer

INDICATIONS AND USAGE

Uses temporarily:
•reduces fever

•relieves minor aches and pains due to:

•the common cold •flu •headache

•sore throat •toothache

Warnings

Liver warning: This product contains acetaminophen.

Severe liver damage may occur if your child takes
•more than 5 doses in 24 hours, which is the maximum daily amount
•with other drugs containing acetaminophen

Allergy alert: acetaminophen may cause severe skin reactions.

Symptoms may include:

•skin reddening •blisters •rash

If a skin reaction occurs, stop use and seek medical help right away

Sore throat warning: if sore throat is severe, persists for more than 2 days, is accompanied or followed by fever, headache, rash, nausea, or vomiting, consult a doctor promptly.

Do not use:
• with any other drug containing acetaminophen (prescription or nonprescription). If you are not sure whether a drug contains acetaminophen, ask a doctor or pharmacist.

• if your child is allergic to acetaminophen or any of the inactive ingredients in this product.

Ask a doctor before use if your child has liver disease

Ask a doctor or pharmacist before use if your child is taking the blood thinning drug warfarin

When using this product do not exceed recommended dose (see overdose warning)

Stop use and ask a doctor if
• pain gets worse or lasts more than 5 days

• fever gets worse or lasts more than 3 days

• new symptoms occur • redness or swelling is present

These could be signs of a serious condition

Keep out of reach of children.

Overdose warning

In case of overdose, get medical help or contact a Poison Control Center right away at (1-800-222-1222). Quick medical attention is critical for adults as well as for children even if you do not notice any signs or symptoms.

Directions
• this product does not contain directions or complete warnings for adult use.

• do not give more than directed (see overdose warning)

• shake well before using

• mL = milliliter
• find right dose on chart below. If possible, use weight todose; otherwise, use age.
• remove the child protective cap and pour your child'sdose into the dosing cup
• repeat dose every 4 hours while symptoms last
• do not give more than 5 times in 24 hours

*or as directed by a doctor

Attention: use only enclosed dosing cup specifically designed for use with this product. Do not use any other dosing device.

Other information

• each 5 mL contains: sodium 4.0 mg
• store between 20-25ºC (68-77ºF)

• do not use if printed inner seal under cap is torn or missing.

Inactive ingredients
anhydrous citric acid, benzyl alcohol, caramel, carboxymethylcellulose sodium, cocoa powder, flavors, glycerin, microcrystalline cellulose, purified water, sodium benzoate, sodium citrate dihydrate, sorbitol solution, sucralose, xanthan gum

Questions or comments?
Call 1-855-848-3284 toll free (English and Spanish)

infirst^+

HEALTHCARE

Manufactured for: Infirst Healthcare Inc., Westport, CT 06880

©2025 Infirst Healthcare Inc.

FLAVORED WITH REAL COCOA

No Parabens.

Free from Synthetic Dyes.

Please visit our website at:

www.DrCocoa.com

4 oz label

Dr. Cocoa®

for Children

Pain + Fever

Acetaminophen (160 mg per 5 ml)

Oral Suspension

Pain Reliever-Fever Reducer

FLAVORED WITH REAL COCOA

Great Chocolate Flavor

Ages 2-11

4 FL OZ (120 mL)

160 mg per 5 mL

8 oz label

Dr. Cocoa®

for Children

Pain + Fever

Acetaminophen (160 mg per 5 ml)

Oral Suspension

Pain Reliever-Fever Reducer

FLAVORED WITH REAL COCOA

Great Chocolate Flavor

Ages 2-11

8 FL OZ (240 mL)

160 mg per 5 mL